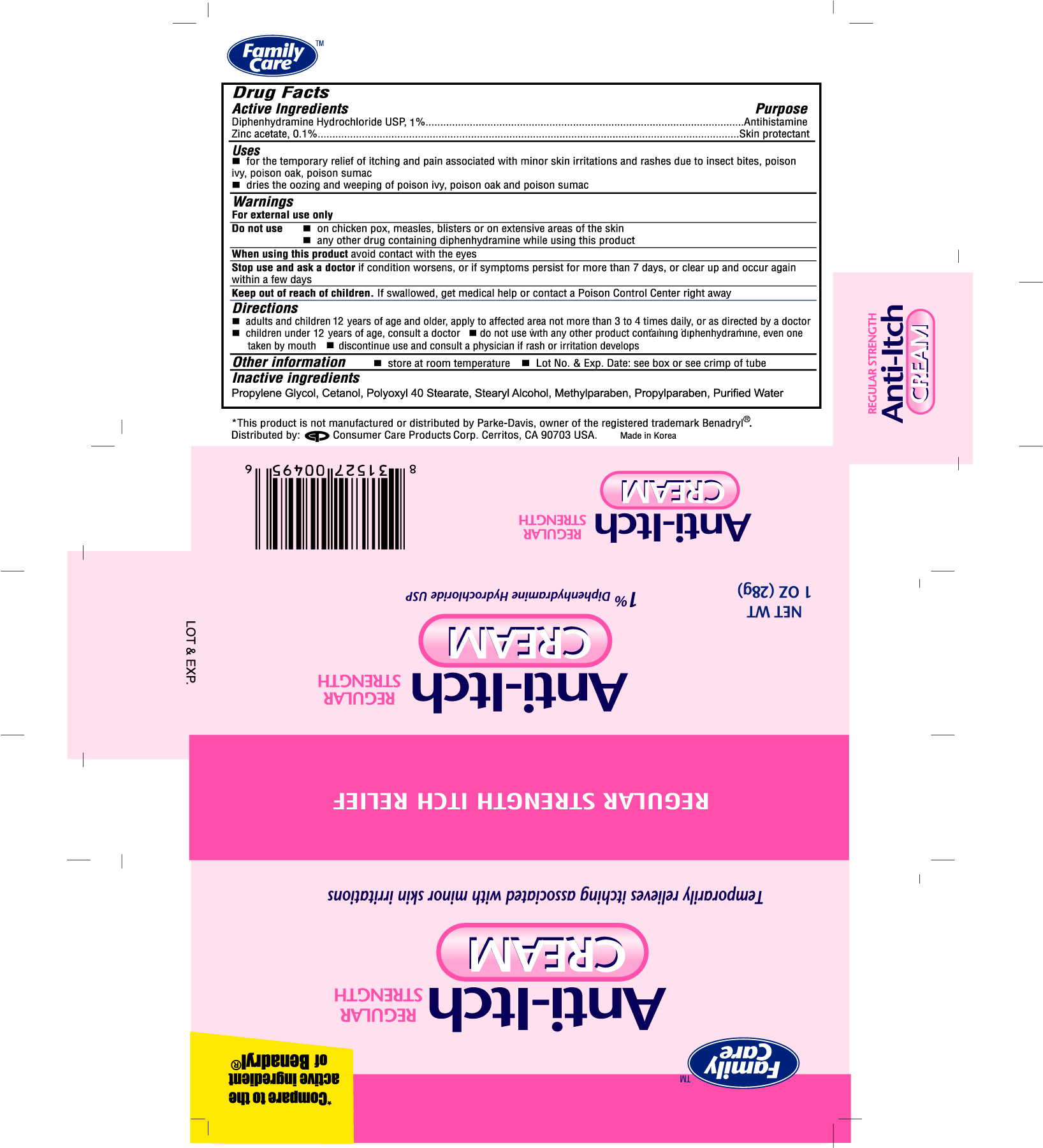 DRUG LABEL: FAMILY CARE ANTI-ITCH 
NDC: 68169-0049 | Form: CREAM
Manufacturer: TAI GUK PHARM. CO., LTD.
Category: otc | Type: HUMAN OTC DRUG LABEL
Date: 20100416

ACTIVE INGREDIENTS: DIPHENHYDRAMINE HYDROCHLORIDE 10 mg/1 g; ZINC ACETATE 1 mg/1 g
INACTIVE INGREDIENTS: PROPYLENE GLYCOL; POLYOXYL 40 STEARATE; STEARYL ALCOHOL; METHYLPARABEN; PROPYLPARABEN; WATER

DRUG FACTS

Active Ingredients Purpose

Diphenhydramine Hydrochloride USP, 1%................................................Antihistamine

Zinc acetate, 0.1%.................................................................................Skin Protectant

Uses

- for the temporary relief of itching and pain associated with minor skin irritations and rashes due to insect bites, poison ivy, poison oak, poison sumac
- dries the oozing and weeping of poison ivy, poison oak and poison sumac

WARNINGS

For external use only

Do not use

- on chicken pox, measles, blisters or on extensive areas of the skin
- any other drug containing diphenhydramine while using this product

When using this product avoid contact with the eyes

Stop use and ask a doctor if condition worsens, or if symptoms persist for more than 7 days, or clear up and occur again within a few days

Keep out of reach of children. If swallowed, get medical help or contact a Poison Control Center right away

Directions

- adults and children 12 years of age and older, apply to affected area not more than 3 to 4 times daily, or as directed by a doctor
- children under 12 years of age, consult a doctor
- do not use with any other product containing diphenhydramine, even one taken by mouth
- discontinue use and consult a physician if rash or irritation develops

Other information

- store at room temperature
- Lot No. and Exp. Date: see box or see crimp of tube

Inactive ingredients

Propylene Glycol, Cetanol, Polyoxyl 40 Stearate, Stearyl Alcohol, Methylparaben, Propylparaben, Purified Water

DOSAGE AND ADMINISTRATION

Distributed by:

Consumer Care Products Corp.

Cerritos, CA 90703 USA

PACKAGE LABEL

Enter section text here